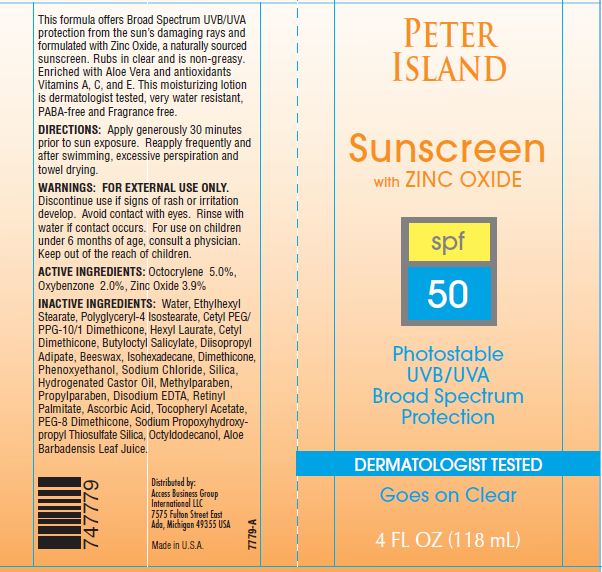 DRUG LABEL: Peter Island Sunscreen
NDC: 10056-700 | Form: LOTION
Manufacturer: ACCESS BUSINESS GROUP INTERNATIONAL LLC
Category: otc | Type: HUMAN OTC DRUG LABEL
Date: 20121120

ACTIVE INGREDIENTS: OCTOCRYLENE 5 g/100 g; OXYBENZONE 2 g/100 g; ZINC OXIDE 3.9 g/100 g
INACTIVE INGREDIENTS: WATER; ETHYLHEXYL STEARATE; POLYGLYCERYL-4 ISOSTEARATE; CETYL PEG/PPG-10/1 DIMETHICONE (HLB 1.5) ; HEXYL LAURATE; BUTYLOCTYL SALICYLATE; DIISOPROPYL ADIPATE; YELLOW WAX; ISOHEXADECANE; DIMETHICONE; PHENOXYETHANOL; SODIUM CHLORIDE; SILICON DIOXIDE; HYDROGENATED CASTOR OIL; METHYLPARABEN; PROPYLPARABEN; EDETATE DISODIUM; VITAMIN A PALMITATE; ASCORBIC ACID; .ALPHA.-TOCOPHEROL ACETATE; OCTYLDODECANOL; ALOE VERA LEAF

Active Ingredients

Octocrylene 5.0%
Oxybenzone 2.0%
Zinc Oxide 3.9%

WARNINGS

FOR EXTERNAL USE ONLY.
Avoid contact with eyes.Rinse with water if contact occurs.

STOP USE

Discontinue use if signs of rash or irritation develop.

ASK DOCTOR

For use on children under 6 moths of age, consult a physician.

Keep out of the reach of children.

Directions

Apply generously 30 minutes prior to sun exposure. Reapply frequently and after swimming, excessive perspiration and towel drying.

This formula offers broad UVB/UVA protection from the sun's damaging rays and formulated with Zinc Oxide, a naturally sourced sunscreen. Rubs in clear and is non-greasy. Enriched with Aloe Vera and antioxidants Vitamins A,C and E. This moisturizing lotion is dermatologist tested, very water resistant, PABA- free and Frangrance free.

Inactive Ingredients

Water, Ethylhexyl Stearate, Cetyl Dimethicone, Butyloctyl Salicylate, Diisopropyl Adipate, Polyglyceryl-4 Isostearate, Cetyl PEG/PPG-10/1 Dimethicone, Hexyl Laurate, Beeswax, Isohexadecane, Sodium Chloride, Silica, Hydrogenated Castor Oil, Dimethicone, Disodium EDTA, PEG-8 Dimethicone, Aloe Barbadensis Leaf Juice Powder, Octyldodecanol, Retinyl Palmitate, Tocopheryl Acetate, Ascorbic Acid, Sodium Propoxyhydroxypropyl Thiosulfate Silica, Phenoxyethanol, Methylparaben, Propylparaben.

Principal Display Panel

PETER ISLAND
Sunscreen with ZINC OXIDE
SPF 50
Photostable UVB/UVA Broad Spectrum Protection
DERMATOLOGIST TESTED
Goes on Clear
4 FL OZ(118mL)